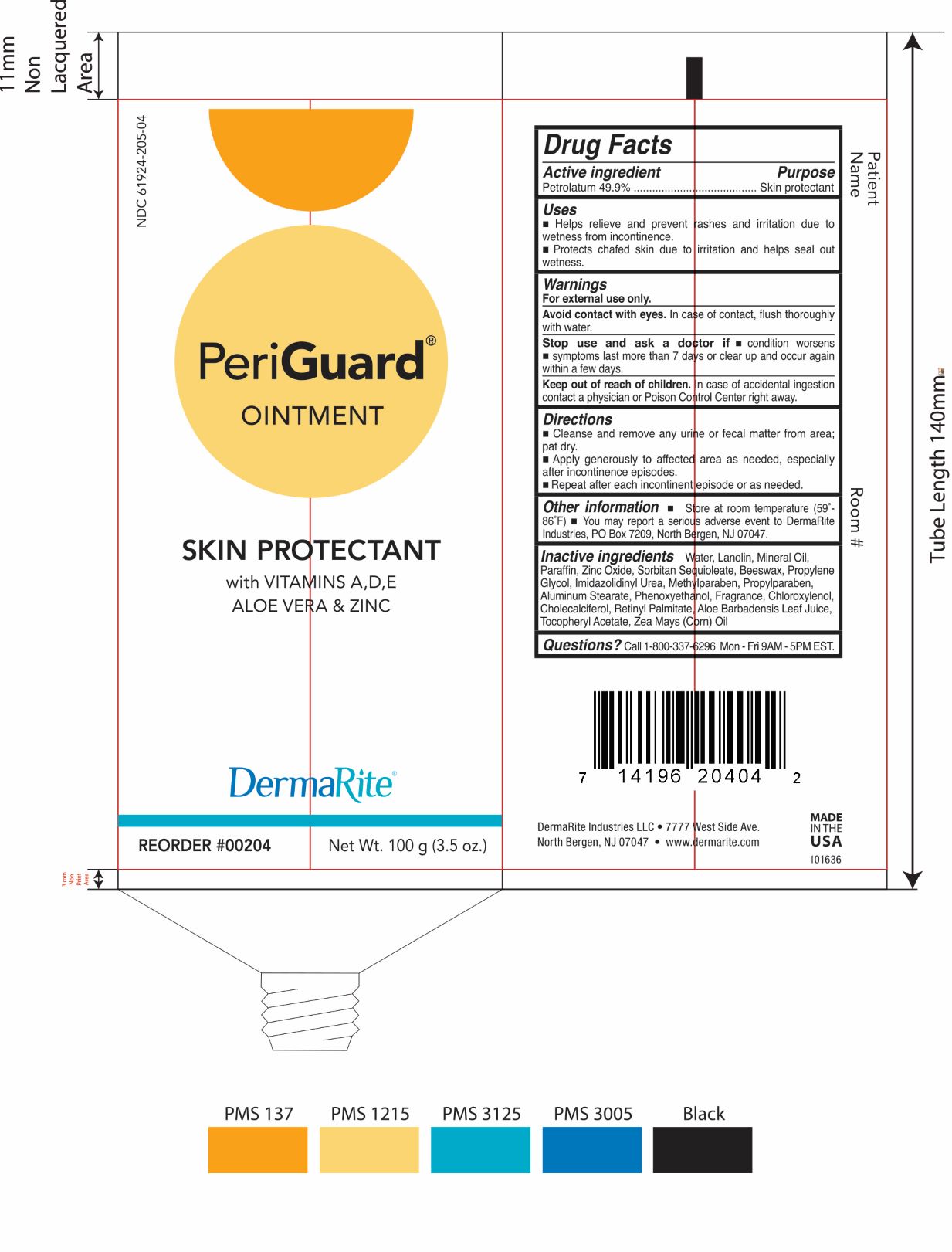 DRUG LABEL: PERIGUARD
NDC: 61924-205 | Form: OINTMENT
Manufacturer: DermaRite Industries, LLC
Category: otc | Type: HUMAN OTC DRUG LABEL
Date: 20241205

ACTIVE INGREDIENTS: PETROLATUM 49.9 g/100 g
INACTIVE INGREDIENTS: ALOE VERA LEAF; ALUMINUM STEARATES; WHITE WAX; CORN OIL; CHOLECALCIFEROL; VITAMIN A PALMITATE; CHLOROXYLENOL; IMIDUREA; METHYLPARABEN; PROPYLENE GLYCOL; PROPYLPARABEN; LANOLIN; MINERAL OIL; PARAFFIN; PHENOXYETHANOL; SORBITAN SESQUIOLEATE; .ALPHA.-TOCOPHEROL ACETATE; ZINC OXIDE; WATER

DRUG LISTING:PERIGUARD OINTMENT

Active Ingredient:

Petrolatum 49.9%

Purpose:

Skin Protectant

Uses:

A moisture barrier that prevents and helps treat skin irritation from urine, feces, perspiration, conditions associated with diaper rash from incontinence.

Warnings:

- For external use only.
- Avoid contact with eyes.In case of contact, flush thoroughly with water.
- Stop use and ask doctor if condition worsens or does not improve within 7 days.
- In case of accidental ingestion contact a physician or Poison Control Center right away.

Warnings:

- Keep out of reach of children. If swallowed, contact a physician or Poison Control Center right away.

Directions:

Cleanse skin gently with a mild cleanser. Pat dry or allow to dry. Apply a thin layer of ointment to the affected area as necessary, or after each incontinent episode or diaper change to promote comfort and long lasting protection.

Other Information:

Store at room temperature (59o- 86oF)

Inactive Ingredients:

Water, Lanolin, Mineral Oil, Paraffin, Zinc Oxide, Sorbitan Sequioleate, Beeswax, Propylene Glycol, Imidazolidinyl Urea, Methylparaben,propylparaben, Aluminum Stearate, Phenoxyethanol, Fragrance, Chloroxylenol,Cholecalciferol, Retinyl Palmitate, Aloe Barbadensis Leaf Juice, Tocopheryl Acetate, Zea Mays (corn) Oil

Questions?

Call 1-800-37-6296